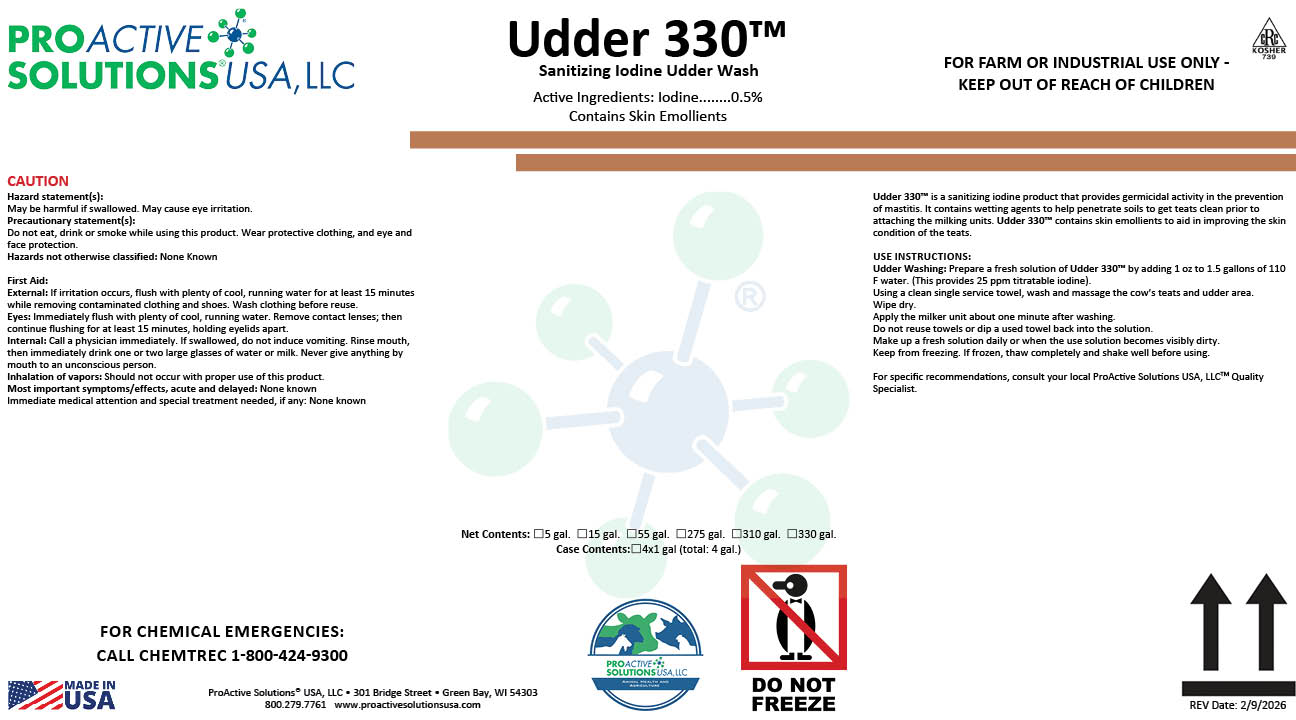 DRUG LABEL: Udder 330
NDC: 63927-4442 | Form: SOLUTION
Manufacturer: ProActive Solutions USA, LLC
Category: animal | Type: OTC ANIMAL DRUG LABEL
Date: 20260210

ACTIVE INGREDIENTS: IODINE 0.5 kg/100 kg

UDDER 330

UDDER 330

Udder 330™ is a sanitizing iodine product that provides germicidal activity in the prevention
of mastitis. It contains wetting agents to help penetrate soils to get teats clean prior to
attaching the milking units. Udder 330™ contains skin emollients to aid in improving the skin
condition of the teats.
USE INSTRUCTIONS:
Udder Washing: Prepare a fresh solution of Udder 330™ by adding 1 oz to 1.5 gallons of 110
F water. (This provides 25 ppm titratable iodine).
Using a clean single service towel, wash and massage the cow’s teats and udder area.
Wipe dry.
Apply the milker unit about one minute after washing.
Do not reuse towels or dip a used towel back into the solution.
Make up a fresh solution daily or when the use solution becomes visibly dirty.
Keep from freezing. If frozen, thaw completely and shake well before using.
For specific recommendations, consult your local ProActive Solutions USA, LLCTM Quality
Specialist.

Hazard statement(s):
May be harmful if swallowed. May cause eye irritation.
Precautionary statement(s):
Do not eat, drink or smoke while using this product. Wear protective clothing, and eye and
face protection.
Hazards not otherwise classified: None Known
First Aid:
External: If irritation occurs, flush with plenty of cool, running water for at least 15 minutes
while removing contaminated clothing and shoes. Wash clothing before reuse.
Eyes: Immediately flush with plenty of cool, running water. Remove contact lenses; then
continue flushing for at least 15 minutes, holding eyelids apart.
Internal: Call a physician immediately. If swallowed, do not induce vomiting. Rinse mouth,
then immediately drink one or two large glasses of water or milk. Never give anything by
mouth to an unconscious person.
Inhalation of vapors: Should not occur with proper use of this product.
Most important symptoms/effects, acute and delayed: None known
Immediate medical attention and special treatment needed, if any: None known